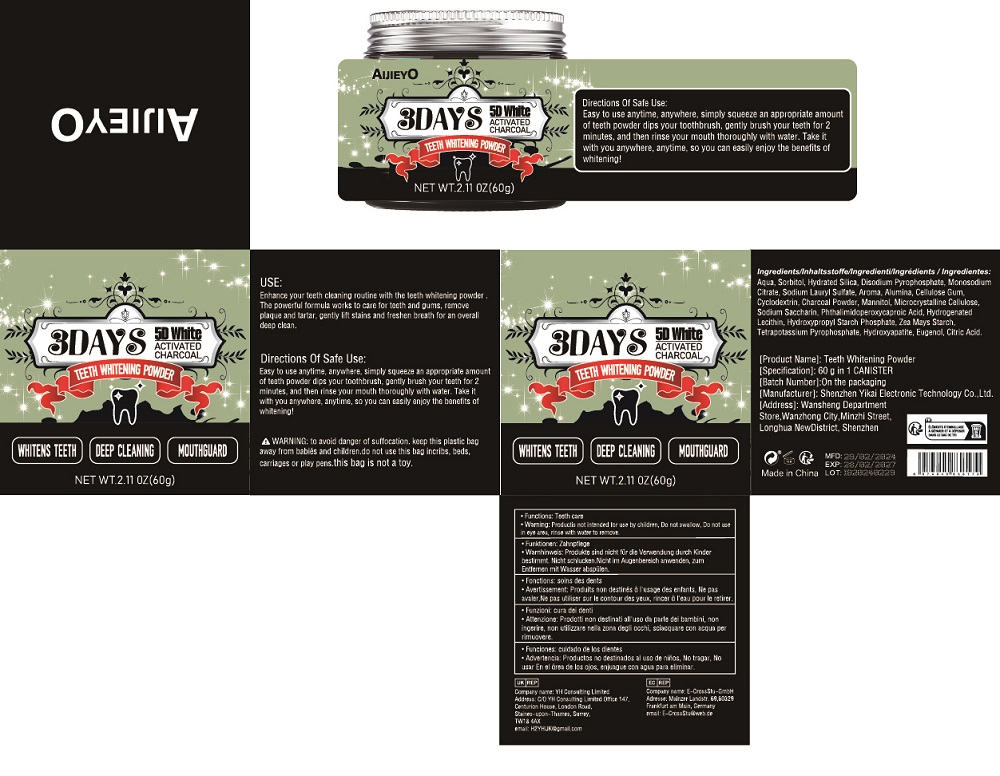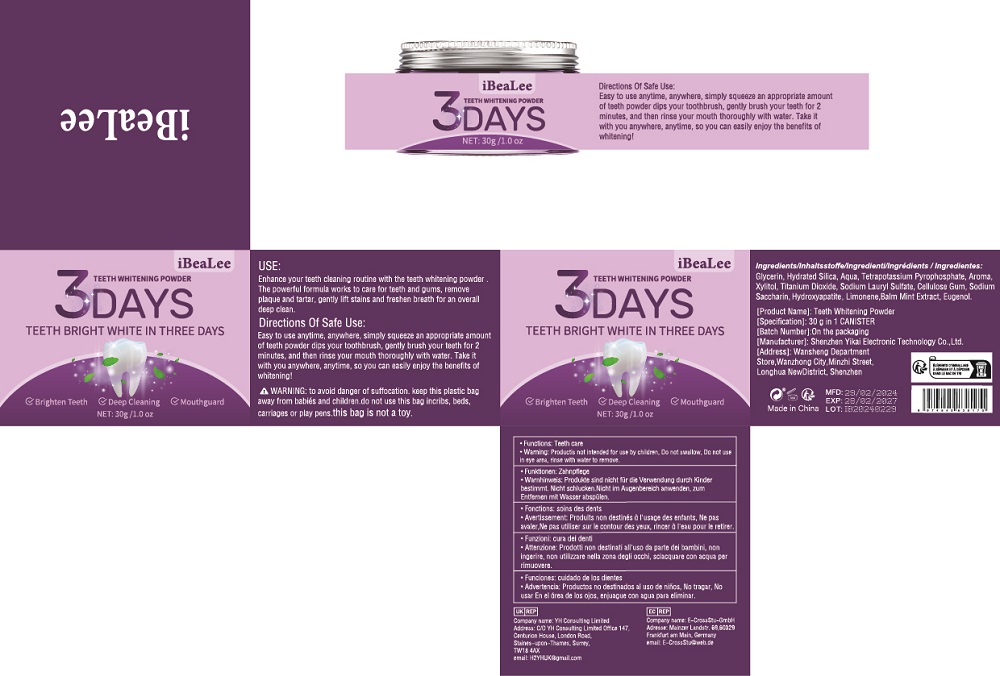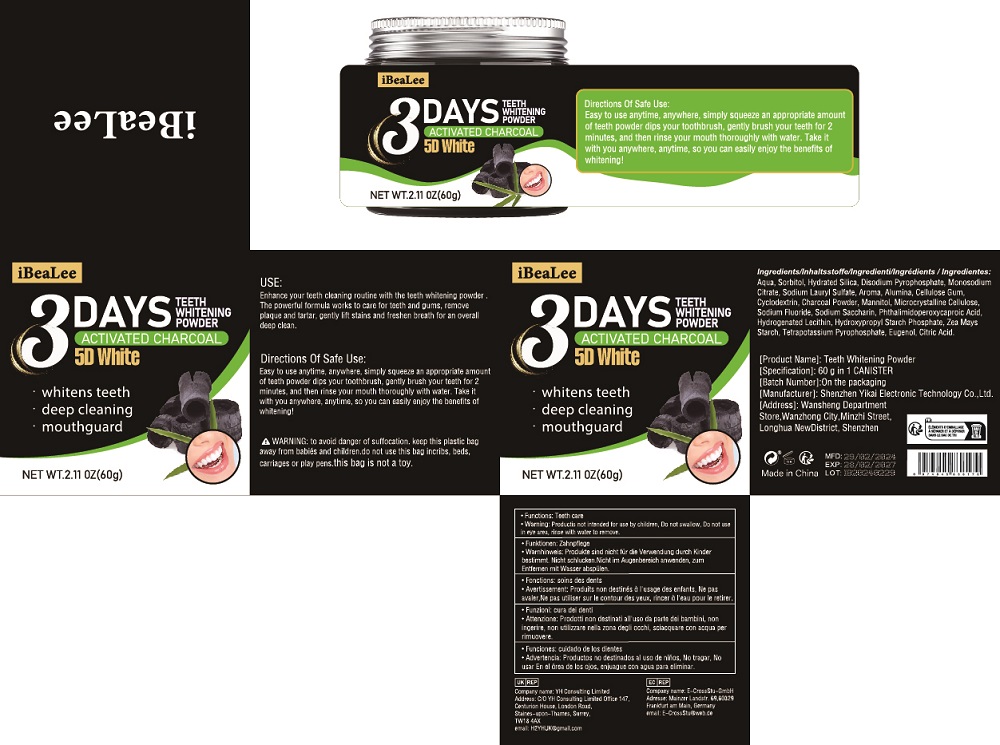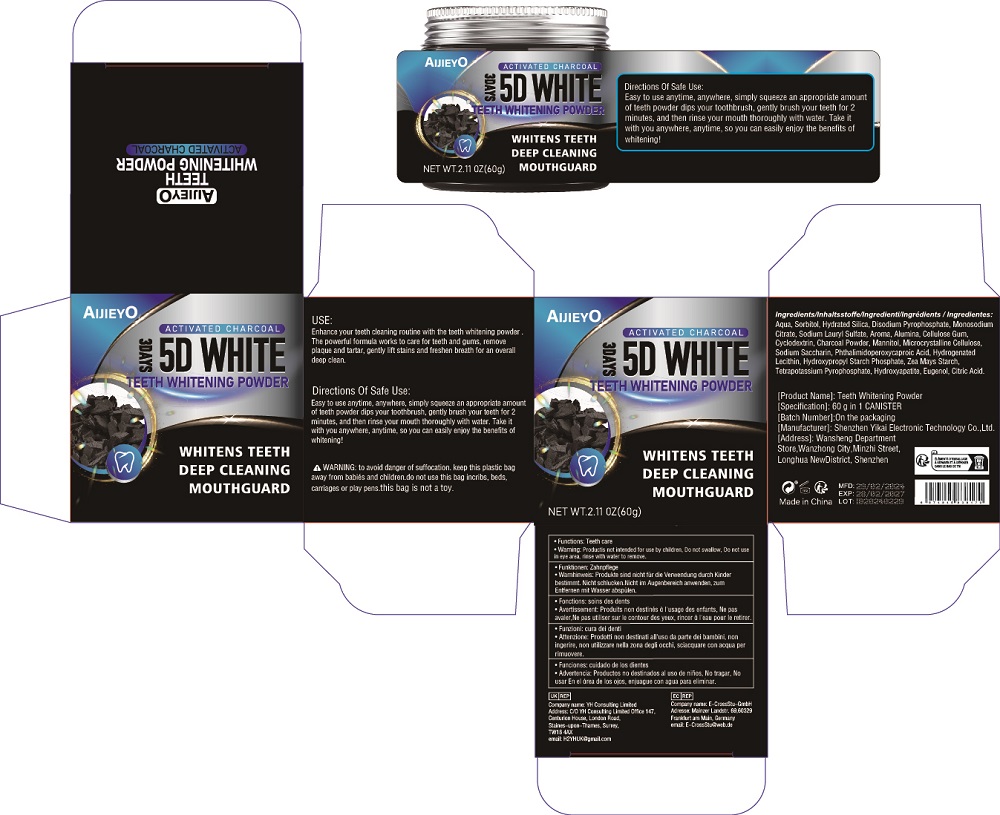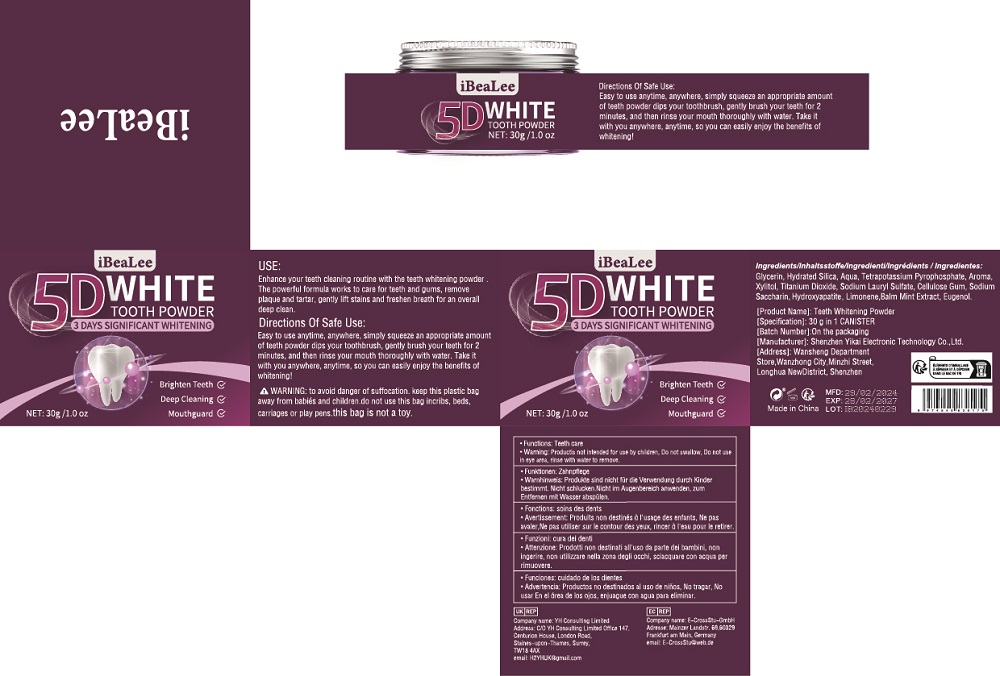 DRUG LABEL: Teeth Whitening Powder
NDC: 84117-010 | Form: POWDER
Manufacturer: Shenzhen Hengkaifeng Commerce and Trade Co., Ltd
Category: otc | Type: HUMAN OTC DRUG LABEL
Date: 20240804

ACTIVE INGREDIENTS: ACTIVATED CHARCOAL 10.94 g/100 g
INACTIVE INGREDIENTS: WATER; SORBITOL; HYDRATED SILICA; SODIUM ACID PYROPHOSPHATE; MONOSODIUM CITRATE; SODIUM LAURYL SULFATE; ALUMINUM OXIDE; CARBOXYMETHYLCELLULOSE SODIUM; CYCLODEXTRINS; MANNITOL; MICROCRYSTALLINE CELLULOSE; MEDIUM-CHAIN TRIGLYCERIDES; SACCHARIN SODIUM; PHTHALIMIDOPEROXYCAPROIC ACID; POTASSIUM PYROPHOSPHATE; EUGENOL; CITRIC ACID MONOHYDRATE; TRIBASIC CALCIUM PHOSPHATE

ACTIVE INGREDIENT

Charcoal Powder 10.94%

Purpose

Teeth Whitening

Use

Enhance your teeth cleaning routine with the teeth whitening powder .
The powerful formula works to care for teeth and gums, remove
plaque and tartar, gently lift stains and freshen breath for an overall
deep clean.

Warnings

WARNING: to avoid danger of suffocation. keep this plastic bag
away from babiés and children.do not use this bag incribs, beds,
carriages or play pens.this bag is not a toy.

Keep Out Of Reach Of Children

Directions Of Safe Use:

Easy to use anytime, anywhere, simply squeeze an appropriate amount
of teeth powder dips your toothbrush, gently brush your teeth for 2
minutes, and then rinse your mouth thoroughly with water. Take it
with you anywhere, anytime, so you can easily enjoy the benefits of
whitening!

Inactive ingredients

Aqua, Sorbitol, Hydrated Silica, Disodium Pyrophosphate, Monosodium
Citrate, Sodium Lauryl Sulfate, Aroma, Alumina, Cellulose Gum,
Cyclodextrin, Mannitol, Microcrystalline Cellulose,
Sodium Saccharin, Phthalimidoperoxycaproic Acid, Hydrogenated
Lecithin, Hydroxypropyl Starch Phosphate, Zea Mays Starch,
Tetrapotassium Pyrophosphate, Hydroxyapatite, Eugenol, Citric Acid.